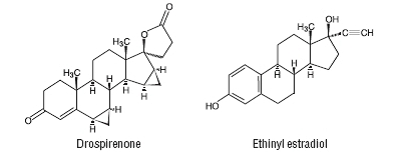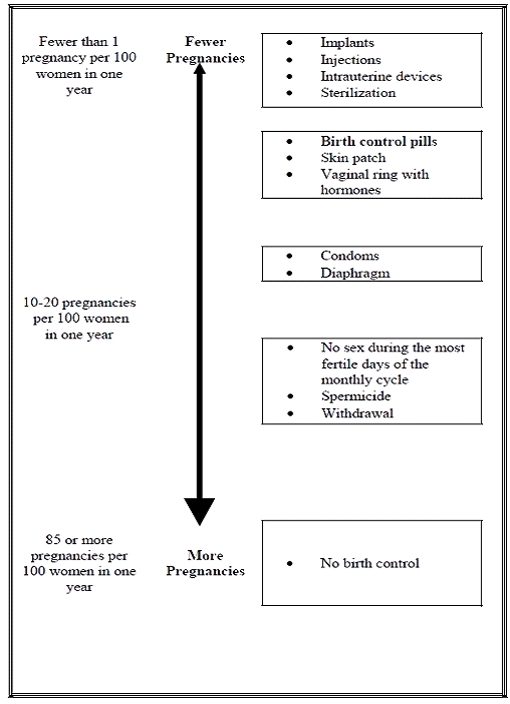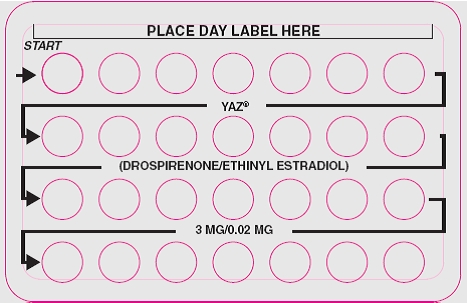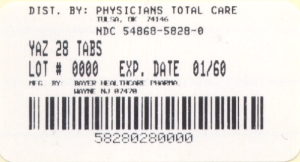 DRUG LABEL: Yaz
NDC: 54868-5828 | Form: KIT | Route: ORAL
Manufacturer: Physicians Total Care, Inc.
Category: prescription | Type: HUMAN PRESCRIPTION DRUG LABEL
Date: 20120315

ACTIVE INGREDIENTS: DROSPIRENONE 3 mg/1 1; ETHINYL ESTRADIOL 0.02 mg/1 1
INACTIVE INGREDIENTS: STARCH, CORN; FERRIC OXIDE RED; HYPROMELLOSES; LACTOSE MONOHYDRATE; MAGNESIUM STEARATE; TALC; TITANIUM DIOXIDE; STARCH, CORN; HYPROMELLOSES; LACTOSE MONOHYDRATE; MAGNESIUM STEARATE; POVIDONE K25; TALC; TITANIUM DIOXIDE

HIGHLIGHTS OF PRESCRIBING INFORMATION

These highlights do not include all the information needed to use YAZ safely and effectively. See full prescribing information for YAZ.
Initial U.S. Approval: 2001

RECENT MAJOR CHANGES

Warnings and Precautions (5.1, 5.7) 3/2011

WARNING: CIGARETTE SMOKING AND SERIOUS CARDIOVASCULAR EVENTS

See full prescribing information for complete boxed warning

- Women over 35 years old who smoke should not use Yaz (4).
- Cigarette smoking increases the risk of serious cardiovascular events from combination oral contraceptive (COC) use. (4)

1 INDICATIONS AND USAGE

Yaz is an estrogen/progestin COC, indicated for use by women to:

- Prevent pregnancy. (1.1)
- Treat symptoms of premenstrual dysphoric disorder (PMDD) for women who choose to use an oral contraceptive for contraception. (1.2)
- Treat moderate acne for women at least 14 years old only if the patient desires an oral contraceptive for birth control. (1.3)

2 DOSAGE AND ADMINISTRATION

- Take one tablet daily by mouth at the same time every day. (2.1)
- Tablets must be taken in the order directed on the blister pack. (2.1)

3 DOSAGE FORMS AND STRENGTHS

Yaz consists of 28 film-coated, biconvex tablets in the following order (3):

- 24 light pink tablets, each containing 3 mg drospirenone (DRSP) and 0.02 mg ethinyl estradiol (EE) as betadex clathrate
- 4 white inert tablets

4 CONTRAINDICATIONS

- Renal impairment or adrenal insufficiency (4)
- A high risk of arterial or venous thrombotic diseases (4)
- Undiagnosed abnormal uterine bleeding (4)
- Breast cancer or other estrogen- or progestin-sensitive cancer (4)
- Liver tumors or liver disease (4)
- Pregnancy (4)

5 WARNINGS AND PRECAUTIONS

- Vascular risks: Stop Yaz if a thrombotic event occurs. Stop at least 4 weeks before and through 2 weeks after major surgery. Start no earlier than 4 weeks after delivery, in women who are not breastfeeding. (5.1)
- Hyperkalemia: DRSP has antimineralocorticoid activity. Do not use in patients predisposed to hyperkalemia. Check serum potassium level during the first treatment cycle in women on long-term treatment with medications that may increase serum potassium. (5.2, 7.3)
- Liver disease: Discontinue Yaz if jaundice occurs. (5.4)
- High blood pressure: Do not prescribe Yaz for women with uncontrolled hypertension or hypertension with vascular disease. (5.5)
- Carbohydrate and lipid metabolic effects: Monitor prediabetic and diabetic women taking Yaz. Consider an alternate contraceptive method for women with uncontrolled dyslipidemia. (5.7)
- Headache: Evaluate significant change in headaches and discontinue Yaz if indicated. (5.8)
- Uterine bleeding: Evaluate irregular bleeding or amenorrhea. (5.9)

6 ADVERSE REACTIONS

- The most frequent (≥ 2%) adverse reactions in contraception and acne clinical trials were: headache/migraine (6.7%), menstrual irregularities (4.7%), nausea/vomiting (4.2%), breast pain/tenderness (4.0%) and mood changes (2.2%).
- The most frequent (≥ 2%) adverse reactions in PMDD clinical trials were: menstrual irregularities (24.9%), nausea (15.8%), headache (13.0%), breast tenderness (10.5%), fatigue (4.2%), irritability (2.8%), decreased libido (2.8%), increased weight (2.5%), and affect lability (2.1%).

To report SUSPECTED ADVERSE REACTIONS, contact Bayer HealthCare Pharmaceuticals Inc. at 1-888-842-2937 or FDA at 1-800-FDA-1088 or www.fda.gov/medwatch

7 DRUG INTERACTIONS

Drugs or herbal products that induce certain enzymes (for example, CYP3A4) may decrease the effectiveness of COCs or increase breakthrough bleeding. Counsel patients to use a back-up or alternative method of contraception when enzyme inducers are used with COCs. (7.1)

8 USE IN SPECIFIC POPULATIONS

Nursing Mothers: Not recommended; can decrease milk production. (8.3)

FULL PRESCRIBING INFORMATION

WARNING: CIGARETTE SMOKING AND SERIOUS CARDIOVASCULAR EVENTS

Cigarette smoking increases the risk of serious cardiovascular events from combination oral contraceptives (COC) use. This risk increases with age, particularly in women over 35 years of age, and with the number of cigarettes smoked. For this reason, COCs should not be used by women who are over 35 years of age and smoke. [See Contraindications (4)].

1 INDICATIONS AND USAGE

1.1 Oral Contraceptive

Yaz is indicated for use by women to prevent pregnancy.

1.2 Premenstrual Dysphoric Disorder (PMDD)

Yaz is also indicated for the treatment of symptoms of premenstrual dysphoric disorder (PMDD) in women who choose to use an oral contraceptive as their method of contraception. The effectiveness of Yaz for PMDD when used for more than three menstrual cycles has not been evaluated.

The essential features of PMDD according to the Diagnostic and Statistical Manual-4th edition (DSM-IV) include markedly depressed mood, anxiety or tension, affective lability, and persistent anger or irritability. Other features include decreased interest in usual activities, difficulty concentrating, lack of energy, change in appetite or sleep, and feeling out of control. Physical symptoms associated with PMDD include breast tenderness, headache, joint and muscle pain, bloating and weight gain. In this disorder, these symptoms occur regularly during the luteal phase and remit within a few days following onset of menses; the disturbance markedly interferes with work or school, or with usual social activities and relationships with others. Diagnosis is made by healthcare providers according to DSM-IV criteria, with symptomatology assessed prospectively over at least two menstrual cycles. In making the diagnosis, care should be taken to rule out other cyclical mood disorders.

Yaz has not been evaluated for the treatment of premenstrual syndrome (PMS).

1.3 Acne

Yaz is indicated for the treatment of moderate acne vulgaris in women at least 14 years of age, who have no known contraindications to oral contraceptive therapy and have achieved menarche. Yaz should be used for the treatment of acne only if the patient desires an oral contraceptive for birth control.

2 DOSAGE AND ADMINISTRATION

2.1 How to Take Yaz

Take one tablet by mouth at the same time every day. The failure rate may increase when pills are missed or taken incorrectly.

To achieve maximum contraceptive and PMDD effectiveness, Yaz must be taken exactly as directed. Single missed pills should be taken as soon as remembered.

2.2 How to Start Yaz

Instruct the patient to begin taking Yaz either on the first day of her menstrual period (Day 1 Start) or on the first Sunday after the onset of her menstrual period (Sunday Start).

Day 1 Start

During the first cycle of Yaz use, instruct the patient to take one light pink Yaz daily, beginning on Day one (1) of her menstrual cycle. (The first day of menstruation is Day one.) She should take one light pink Yaz daily for 24 consecutive days, followed by one white inert tablet daily on days 25 through 28. Yaz should be taken in the order directed on the package at the same time each day, preferably after the evening meal or at bedtime with some liquid, as needed. Yaz can be taken without regard to meals. If Yaz is first taken later than the first day of the menstrual cycle, Yaz should not be considered effective as a contraceptive until after the first 7 consecutive days of product administration. Instruct the patient to use a non-hormonal contraceptive as back-up during the first 7 days. The possibility of ovulation and conception prior to initiation of medication should be considered.

Sunday Start

During the first cycle of Yaz use, instruct the patient to take one light pink Yaz daily, beginning on the first Sunday after the onset of her menstrual period. She should take one light pink Yaz daily for 24 consecutive days, followed by one white inert tablet daily on days 25 through 28. Yaz should be taken in the order directed on the package at the same time each day, preferably after the evening meal or at bedtime with some liquid, as needed. Yaz can be taken without regard to meals. Yaz should not be considered effective as a contraceptive until after the first 7 consecutive days of product administration. Instruct the patient to use a non-hormonal contraceptive as back-up during the first 7 days. The possibility of ovulation and conception prior to initiation of medication should be considered.

The patient should begin her next and all subsequent 28-day regimens of Yaz on the same day of the week that she began her first regimen, following the same schedule. She should begin taking her light pink tablets on the next day after ingestion of the last white tablet, regardless of whether or not a menstrual period has occurred or is still in progress. Anytime a subsequent cycle of Yaz is started later than the day following administration of the last white tablet, the patient should use another method of contraception until she has taken a light pink Yaz daily for seven consecutive days.

When switching from a different birth control pill

When switching from another birth control pill, Yaz should be started on the same day that a new pack of the previous oral contraceptive would have been started.

When switching from a method other than a birth control pill

When switching from a transdermal patch or vaginal ring, Yaz should be started when the next application would have been due. When switching from an injection, Yaz should be started when the next dose would have been due. When switching from an intrauterine contraceptive or an implant, Yaz should be started on the day of removal.

Withdrawal bleeding usually occurs within 3 days following the last light pink tablet. If spotting or breakthrough bleeding occurs while taking Yaz, instruct the patient to continue taking her Yaz by the regimen described above. Counsel her that this type of bleeding is usually transient and without significance; however, advise her that if the bleeding is persistent or prolonged, she should consult her healthcare provider.

Although the occurrence of pregnancy is low if Yaz is taken according to directions, if withdrawal bleeding does not occur, consider the possibility of pregnancy. If the patient has not adhered to the prescribed dosing schedule (missed one or more active tablets or started taking them on a day later than she should have), consider the possibility of pregnancy at the time of the first missed period and take appropriate diagnostic measures. If the patient has adhered to the prescribed regimen and misses two consecutive periods, rule out pregnancy. Discontinue Yaz if pregnancy is confirmed.

The risk of pregnancy increases with each active light pink tablet missed. For additional patient instructions regarding missed pills, see the "WHAT TO DO IF YOU MISS PILLS" section in the FDA Approved Patient Labeling which follows. If breakthrough bleeding occurs following missed tablets, it will usually be transient and of no consequence. If the patient misses one or more white tablets, she should still be protected against pregnancy provided she begins taking a new cycle of light pink tablets on the proper day.

For postpartum women who do not breastfeed or after a second trimester abortion, start Yaz no earlier than 4 weeks postpartum due to the increased risk of thromboembolism. If the patient starts on Yaz postpartum and has not yet had a period, evaluate for possible pregnancy, and instruct her to use an additional method of contraception until she has taken Yaz for 7 consecutive days.

2.3 Advice in case of Gastrointestinal Disturbances

In case of severe vomiting or diarrhea, absorption may not be complete and additional contraceptive measures should be taken. If vomiting occurs within 3–4 hours after tablet-taking, this can be regarded as a missed tablet.

3 DOSAGE FORMS AND STRENGTHS

Yaz (drospirenone/ethinyl estradiol tablets) is available in blister packs.

Each blister pack (28 film-coated tablets) contains in the following order:

- 24 light pink tablets each containing 3 mg drospirenone (DRSP) and 0.02 mg ethinyl estradiol (EE) as betadex clathrate
- 4 white inert tablets

4 CONTRAINDICATIONS

Do not prescribe Yaz to women who are known to have the following:

- Renal impairment
- Adrenal insufficiency
- A high risk of arterial or venous thrombotic diseases. Examples include women who are known to:
  - Smoke, if over age 35 [see Boxed Warning and Warnings and Precautions (5.1)]
  - Have deep vein thrombosis or pulmonary embolism, now or in the past [see Warnings and Precautions (5.1)]
  - Have cerebrovascular disease [see Warnings and Precautions (5.1)]
  - Have coronary artery disease [see Warnings and Precautions (5.1)]
  - Have thrombogenic valvular or thrombogenic rhythm diseases of the heart (for example, subacute bacterial endocarditis with valvular disease, or atrial fibrillation) [see Warnings and Precautions (5.1)]
  - Have inherited or acquired hypercoagulopathies [see Warnings and Precautions (5.1)]
  - Have uncontrolled hypertension [see Warnings and Precautions (5.5)]
  - Have diabetes mellitus with vascular disease [see Warnings and Precautions (5.7)]
  - Have headaches with focal neurological symptoms or have migraine headaches with or without aura if over age 35 [see Warnings and Precautions (5.8)]
- Undiagnosed abnormal uterine bleeding [see Warnings and Precautions (5.9)]
- Breast cancer or other estrogen- or progestin-sensitive cancer, now or in the past [see Warnings and Precautions (5.3)]
- Liver tumors, benign or malignant, or liver disease [see Warnings and Precautions (5.4) and Use in Specific Populations (8.7)]
- Pregnancy, because there is no reason to use COCs during pregnancy [see Warnings and Precautions (5.10) and Use in Specific Populations (8.1)]

5 WARNINGS AND PRECAUTIONS

5.1 Thromboembolic Disorders and Other Vascular Problems

Stop Yaz if an arterial or venous thrombotic (VTE) event occurs.

The use of COCs increases the risk of venous thromboembolism. However, pregnancy increases the risk of venous thromboembolism as much or more than the use of COCs. The risk of venous thromboembolism in women using COCs has been estimated to be 3 to 9 per 10,000 woman-years. The risk of VTE is highest during the first year of use. Interim data from a large, prospective cohort safety study of various COCs suggest that this increased risk, as compared to that in non-COC users, is greatest during the first 6 months of COC use. Interim data from this safety study indicate that the greatest risk of VTE is present after initially starting a COC or restarting (following a 4 week or greater pill-free interval) the same or a different COC.

Use of COCs also increases the risk of arterial thromboses such as strokes and myocardial infarctions, especially in women with other risk factors for these events.

The risk of thromboembolic disease due to oral contraceptives gradually disappears after COC use is discontinued.

If feasible, stop Yaz at least 4 weeks before and through 2 weeks after major surgery or other surgeries known to have an elevated risk of thromboembolism.

Start Yaz no earlier than 4 weeks after delivery, in women who are not breastfeeding. The risk of postpartum thromboembolism decreases after the third postpartum week, whereas the risk of ovulation increases after the third postpartum week.

COCs have been shown to increase both the relative and attributable risks of cerebrovascular events (thrombotic and hemorrhagic strokes), although, in general, the risk is greatest among older (>35 years of age), hypertensive women who also smoke. COCs also increase the risk for stroke in women with other underlying risk factors.

Oral contraceptives must be used with caution in women with cardiovascular disease risk factors.

Stop Yaz if there is unexplained loss of vision, proptosis, diplopia, papilledema, or retinal vascular lesions. Evaluate for retinal vein thrombosis immediately. [See Adverse Reactions (6).]

Epidemiologic studies including a DRSP-containing COC

Several studies have investigated the relative risks of thromboembolism in women using a different DRSP-containing COC (Yasmin, which contains 0.03 mg of EE and 3 mg of DRSP) compared to those in women using COCs containing other progestins. Two prospective cohort studies, both evaluating the risk of venous and arterial thromboembolism and death, were initiated at the time of Yasmin approval.^1,2 The first (EURAS) showed the risk of thromboembolism (particularly venous thromboembolism) and death in Yasmin users to be comparable to that of other oral contraceptive preparations, including those containing levonorgestrel (a so-called second generation COC). The second prospective cohort study (Ingenix) also showed a comparable risk of thromboembolism in Yasmin users compared to users of other COCs, including those containing levonorgestrel. In the second study, COC comparator groups were selected based on their having similar characteristics to those being prescribed Yasmin.

Two additional epidemiological studies, one case-control study (van Hylckama Vlieg et al.^3) and one retrospective cohort study (Lidegaard et al.^4) suggested that the risk of venous thromboembolism occurring in Yasmin users was higher than that for users of levonorgestrel-containing COCs and lower than that for users of desogestrel/gestodene-containing COCs (so-called third generation COCs). In the case-control study, however, the number of Yasmin cases was very small (1.2% of all cases) making the risk estimates unreliable. The relative risk for Yasmin users in the retrospective cohort study was greater than that for users of other COC products when considering women who used the products for less than one year. However, these one-year estimates may not be reliable because the analysis may include women of varying risk levels. Among women who used the product for 1 to 4 years, the relative risk was similar for users of Yasmin to that for users of other COC products.

5.2 Hyperkalemia

Yaz contains 3 mg of the progestin DRSP which has antimineralocorticoid activity, including the potential for hyperkalemia in high-risk patients, comparable to a 25 mg dose of spironolactone. Yaz should not be used in patients with conditions that predispose to hyperkalemia (that is, renal impairment, hepatic dysfunction and adrenal insufficiency). Women receiving daily, long-term treatment for chronic conditions or diseases with medications that may increase serum potassium should have their serum potassium level checked during the first treatment cycle. Medications that may increase serum potassium include ACE inhibitors, angiotensin-II receptor antagonists, potassium-sparing diuretics, potassium supplementation, heparin, aldosterone antagonists, and NSAIDS.

5.3 Carcinoma of the Breasts and Reproductive Organs

Women who currently have or have had breast cancer should not use Yaz because breast cancer is a hormonally-sensitive tumor.

There is substantial evidence that COCs do not increase the incidence of breast cancer. Although some past studies have suggested that COCs might increase the incidence of breast cancer, more recent studies have not confirmed such findings.

Some studies suggest that COCs are associated with an increase in the risk of cervical cancer or intraepithelial neoplasia. However, there is controversy about the extent to which these findings may be due to differences in sexual behavior and other factors.

5.4 Liver Disease

Discontinue Yaz if jaundice develops. Steroid hormones may be poorly metabolized in patients with impaired liver function. Acute or chronic disturbances of liver function may necessitate the discontinuation of COC use until markers of liver function return to normal and COC causation has been excluded.

Hepatic adenomas are associated with COC use. An estimate of the attributable risk is 3.3 cases/100,000 COC users. Rupture of hepatic adenomas may cause death through intra-abdominal hemorrhage.

Studies have shown an increased risk of developing hepatocellular carcinoma in long-term (>8 years) COC users. However, the attributable risk of liver cancers in COC users is less than one case per million users.

Oral contraceptive-related cholestasis may occur in women with a history of pregnancy-related cholestasis. Women with a history of COC-related cholestasis may have the condition recur with subsequent COC use.

5.5 High Blood Pressure

For women with well-controlled hypertension, monitor blood pressure and stop Yaz if blood pressure rises significantly. Women with uncontrolled hypertension or hypertension with vascular disease should not use COCs.

An increase in blood pressure has been reported in women taking COCs, and this increase is more likely in older women and with extended duration of use. The incidence of hypertension increases with increasing concentration of progestin.

5.6 Gallbladder Disease

Studies suggest a small increased relative risk of developing gallbladder disease among COC users.

5.7 Carbohydrate and Lipid Metabolic Effects

Carefully monitor prediabetic and diabetic women who are taking Yaz. COCs may decrease glucose intolerance in a dose-related fashion.

Consider alternative contraception for women with uncontrolled dyslipidemias. A small proportion of women will have adverse lipid changes while on COC’s.

Women with hypertriglyceridemia, or a family history thereof, may be at an increased risk of pancreatitis when using COCs.

5.8 Headache

If a woman taking Yaz develops new headaches that are recurrent, persistent, or severe, evaluate the cause and discontinue Yaz if indicated.

An increase in frequency or severity of migraine during COC use (which may be prodromal of a cerebrovascular event) may be a reason for immediate discontinuation of the COC.

5.9 Bleeding Irregularities

Unscheduled (breakthrough or intracyclic) bleeding and spotting sometimes occur in patients on COCs, especially during the first three months of use. If bleeding persists or occurs after previously regular cycles, check for causes such as pregnancy or malignancy. If pathology and pregnancy are excluded, bleeding irregularities may resolve over time or with a change to a different COC.

Based on patient diaries from two contraceptive clinical trials of Yaz, 8 to 25% of women experienced unscheduled bleeding per 28-day cycle. A total of 12 subjects out of 1,056 (1.1%) discontinued due to menstrual disorders including intermenstrual bleeding, menorrhagia, and metrorrhagia.

Women who use Yaz may experience absence of withdrawal bleeding, even if they are not pregnant. Based on subject diaries from contraception trials for up to 13 cycles, 6 to 10% of women experienced cycles with no withdrawal bleeding. Some women may encounter post-pill amenorrhea or oligomenorrhea, especially when such a condition was pre-existent.

If withdrawal bleeding does not occur, consider the possibility of pregnancy. If the patient has not adhered to the prescribed dosing schedule (missed one or more active tablets or started taking them on a day later than she should have), consider the possibility of pregnancy at the time of the first missed period and take appropriate diagnostic measures. If the patient has adhered to the prescribed regimen and misses two consecutive periods, rule out pregnancy.

5.10 COC Use Before or During Early Pregnancy

Extensive epidemiological studies have revealed no increased risk of birth defects in women who have used oral contraceptives prior to pregnancy. Studies also do not suggest a teratogenic effect, particularly in so far as cardiac anomalies and limb-reduction defects are concerned, when taken inadvertently during early pregnancy.

The administration of oral contraceptives to induce withdrawal bleeding should not be used as a test for pregnancy [see Use in Specific Populations (8.1)].

5.11 Depression

Women with a history of depression should be carefully observed and Yaz discontinued if depression recurs to a serious degree.

5.12 Interference with Laboratory Tests

The use of COCs may change the results of some laboratory tests, such as coagulation factors, lipids, glucose tolerance, and binding proteins. Women on thyroid hormone replacement therapy may need increased doses of thyroid hormone because serum concentrations of thyroid-binding globulin increase with use of COCs. DRSP causes an increase in plasma renin activity and plasma aldosterone induced by its mild antimineralocorticoid activity.

5.13 Monitoring

A woman who is taking COCs should have a yearly visit with her healthcare provider for a blood pressure check and for other indicated healthcare.

5.14 Other Conditions

In women with hereditary angioedema, exogenous estrogens may induce or exacerbate symptoms of angioedema. Chloasma may occasionally occur, especially in women with a history of chloasma gravidarum. Women with a tendency to chloasma should avoid exposure to the sun or ultraviolet radiation while taking COCs.

6 ADVERSE REACTIONS

The following serious adverse reactions with the use of COCs are discussed elsewhere in the labeling:

- Serious cardiovascular events and smoking [see Boxed Warning and Warnings and Precautions (5.1)]
- Vascular events [see Warnings and Precautions (5.1)]
- Liver disease [see Warnings and Precautions (5.3)]

Adverse reactions commonly reported by COC users are:

- Irregular uterine bleeding
- Nausea
- Breast tenderness
- Headache

6.1 Clinical Trials Experience

Because clinical trials are conducted under widely varying conditions, adverse reaction rates observed in the clinical trials of a drug cannot be directly compared to rates in the clinical trials of another drug and may not reflect the rates observed in clinical practice.

Contraception and Acne Clinical Trials

The data provided reflect the experience with the use of Yaz in the adequate and well-controlled studies for contraception (N=1,056) and for moderate acne vulgaris (N=536).

For contraception, a Phase 3, multicenter, multinational, open-label study was conducted to evaluate safety and efficacy up to one year in 1,027 women aged 17 – 36 who took at least one dose of Yaz. A second Phase 3 study was a single center, open-label, active-controlled study to evaluate the effect of 7 28-day cycles of Yaz on carbohydrate metabolism, lipids and hemostasis in 29 women aged 18–35. For acne, two multicenter, double-blind, randomized, placebo-controlled studies, in 536 women aged 14–45 with moderate acne vulgaris who took at least one dose of Yaz, evaluated the safety and efficacy during up to 6 cycles.

The adverse reactions seen across the 2 indications overlapped, and are reported using the frequencies from the pooled dataset. The most common adverse reactions (≥ 2% of users) were: headache/migraine (6.7%), menstrual irregularities (including vaginal hemorrhage [primarily spotting] and metrorrhagia (4.7%), nausea/vomiting (4.2%), breast pain/tenderness (4%) and mood changes (mood swings, depression, depressed mood and affect lability) (2.2%).

PMDD Clinical Trials

Safety data from trials for the indication of PMDD are reported separately due to differences in study design and setting in the Contraception and Acne studies as compared to the PMDD clinical program.

Two (one parallel and one crossover designed) multicenter, double-blind, randomized, placebo-controlled trials for the secondary indication of treating the symptoms of PMDD evaluated safety and efficacy of Yaz during up to 3 cycles among 285 women aged 18–42, diagnosed with PMDD and who took at least one dose of Yaz.

Common adverse reactions (≥ 2% of users) were: menstrual irregularities (including vaginal hemorrhage [primarily spotting] and metrorrhagia) (24.9%), nausea (15.8%), headache (13%), breast tenderness (10.5%), fatigue (4.2%), irritability (2.8%), decreased libido (2.8%), increased weight (2.5%), and affect lability (2.1%).

Adverse Reactions (≥1%) Leading to Study Discontinuation:

Contraception Clinical Trials

Of 1,056 women, 6.6% discontinued from the clinical trials due to an adverse reaction; the most frequent adverse reactions leading to discontinuation were headache/migraine (1.6%) and nausea/vomiting (1%).

Acne Clinical Trials

Of 536 women, 5.4% discontinued from the clinical trials due to an adverse reaction; the most frequent adverse reaction leading to discontinuation was menstrual irregularities (including menometrorrhagia, menorrhagia, metrorrhagia and vaginal hemorrhage) (2.2%) .

PMDD Clinical Trials

Of 285 women, 11.6% discontinued from the clinical trials due to an adverse reaction; the most frequent adverse reactions leading to discontinuation were: nausea/vomiting (4.6%), menstrual irregularity (including vaginal hemorrhage, menorrhagia, menstrual disorder, menstruation irregular and metrorrhagia) (4.2%), fatigue (1.8%), breast tenderness (1.4%), depression (1.4%), headache (1.1%), and irritability (1.1%).

Serious Adverse Reactions:

Contraception Clinical Trials: migraine and cervical dysplasia

Acne Clinical Trials: none reported in the clinical trials

PMDD Clinical Trials: cervical dysplasia

6.2 Postmarketing Experience

The following adverse reactions have been identified during post approval use of Yaz. Because these reactions are reported voluntarily from a population of uncertain size, it is not always possible to reliably estimate their frequency or establish a causal relationship to drug exposure.

Adverse reactions are grouped into System Organ Classes, and ordered by frequency.

Vascular disorders: Venous and arterial thromboembolic events (including pulmonary emboli, deep vein thrombosis, cerebral thrombosis, retinal thrombosis, myocardial infarction and stroke), hypertension (including hypertensive crisis)

Hepatobiliary disorders: Gallbladder disease, liver function disturbances, liver tumors

Immune system disorders: Hypersensitivity (including anaphylactic reaction)

Metabolism and nutrition disorders: Hyperkalemia, hypertriglyceridemia, changes in glucose tolerance or effect on peripheral insulin resistance (including diabetes mellitus)

Skin and subcutaneous tissue disorders: Chloasma, angioedema, erythema nodosum, erythema multiforme

Gastrointestinal disorders: Inflammatory bowel disease

Musculoskeletal and connective tissue disorders: Systemic lupus erythematosus

7 DRUG INTERACTIONS

Consult the labeling of all concurrently-used drugs to obtain further information about interactions with hormonal contraceptives or the potential for enzyme alterations.

7.1 Effects of Other Drugs on Combined Hormonal Contraceptives

Substances diminishing the efficacy of COCs: Drugs or herbal products that induce certain enzymes, including CYP3A4, may decrease the effectiveness of COCs or increase breakthrough bleeding. Some drugs or herbal products that may decrease the effectiveness of hormonal contraceptives include phenytoin, barbiturates, carbamazepine, bosentan, felbamate, griseofulvin, oxcarbazepine, rifampicin, topiramate and products containing St. John’s wort. Interactions between oral contraceptives and other drugs may lead to breakthrough bleeding and/or contraceptive failure. Counsel women to use an alternative method of contraception or a back-up method when enzyme inducers are used with COCs, and to continue back-up contraception for 28 days after discontinuing the enzyme inducer to ensure contraceptive reliability.

Substances increasing the plasma levels of COCs: Co-administration of atorvastatin and certain COCs containing EE increase AUC values for EE by approximately 20%. Ascorbic acid and acetaminophen may increase plasma EE levels, possibly by inhibition of conjugation. CYP3A4 inhibitors such as itraconazole or ketoconazole may increase plasma hormone levels.

HIV protease inhibitors and non-nucleoside reverse transcriptase inhibitors : Significant changes (increase and decrease) in plasma levels of estrogen and progestin have been noted in some cases of co-administration with HIV protease inhibitors or with non-nucleoside reverse transcriptase inhibitors.

Antibiotics: There have been reports of pregnancy while taking hormonal contraceptives and antibiotics, but clinical pharmacokinetic studies have not shown consistent effects of antibiotics on plasma concentrations of synthetic steroids.

Effect on DRSP: The main metabolites of DRSP in human plasma are generated without involvement of the cytochrome P450 system. Inhibitors of this enzyme system are therefore unlikely to influence the metabolism of DRSP.

7.2 Effects of Combined Oral Contraceptives on Other Drugs

COCs containing EE may inhibit the metabolism of other compounds. COCs have been shown to significantly decrease plasma concentrations of lamotrigine, likely due to induction of lamotrigine glucuronidation. This may reduce seizure control; therefore, dosage adjustments of lamotrigine may be necessary. Consult the labeling of the concurrently-used drug to obtain further information about interactions with COCs or the potential for enzyme alterations.

In vitro and clinical studies did not indicate an inhibitory potential of DRSP towards human CYP450 enzymes at clinically relevant concentrations [see Clinical Pharmacology (12.3)].

7.3 Interactions that Have the Potential to Increase Serum Potassium

There is a potential for an increase in serum potassium in women taking Yaz with other drugs that may increase serum potassium [see Warnings and Precautions (5.2) and Clinical Pharmacology (12.3)].

8 USE IN SPECIFIC POPULATIONS

8.1 Pregnancy

There is little or no increased risk of birth defects in women who inadvertently use COCs during early pregnancy. Epidemiologic studies and meta-analyses have not found an increased risk of genital or non-genital birth defects (including cardiac anomalies and limb-reduction defects) following exposure to low dose COCs prior to conception or during early pregnancy.

The administration of COCs to induce withdrawal bleeding should not be used as a test for pregnancy. COCs should not be used during pregnancy to treat threatened or habitual abortion.

Women who do not breastfeed may start COCs no earlier than four weeks postpartum.

8.3 Nursing Mothers

When possible, advise the nursing mother to use other forms of contraception until she has weaned her child. Estrogen-containing COCs can reduce milk production in breastfeeding mothers. This is less likely to occur once breastfeeding is well-established; however, it can occur at any time in some women. Small amounts of oral contraceptive steroids and/or metabolites are present in breast milk.

After oral administration of 3 mg DRSP/0.03 mg EE (Yasmin) tablets, about 0.02% of the DRSP dose was excreted into the breast milk of postpartum women within 24 hours. This results in a maximal daily dose of about 0.003 mg DRSP in an infant.

8.4 Pediatric Use

Safety and efficacy of Yaz has been established in women of reproductive age. Safety and efficacy are expected to be the same for postpubertal adolescents under the age of 18 and for users 18 years and older. Use of this product before menarche is not indicated.

8.5 Geriatric Use

Yaz has not been studied in postmenopausal women and is not indicated in this population.

8.6 Patients with Renal Impairment

Yaz is contraindicated in patients with renal impairment [see Contraindications (4) and Warnings and Precautions (5.2)].

In subjects with mild renal impairment (creatinine clearance CLcr, 50–80 mL/min), serum DRSP levels were comparable to those in subjects with normal renal function (CLcr, >80 mL/min). In subjects with moderate renal impairment (CLcr, 30–50 mL/min), serum DRSP levels were on average 37% higher than those in the group with normal renal function. In addition, there is a potential to develop hyperkalemia in subjects with renal impairment whose serum potassium is in the upper reference range, and who are concomitantly using potassium sparing drugs [see Clinical Pharmacology (12.3)].

8.7 Patients with Hepatic Impairment

Yaz is contraindicated in patients with hepatic disease [see Contraindications (4) and Warnings and Precautions (5.4)] . The mean exposure to DRSP in women with moderate liver impairment is approximately three times higher than the exposure in women with normal liver function. Yaz has not been studied in women with severe hepatic impairment.

10 OVERDOSAGE

There have been no reports of serious ill effects from overdose, including ingestion by children. Overdosage may cause withdrawal bleeding in females and nausea.

DRSP is a spironolactone analogue which has antimineralocorticoid properties. Serum concentration of potassium and sodium, and evidence of metabolic acidosis, should be monitored in cases of overdose.

11 DESCRIPTION

Yaz (drospirenone/ethinyl estradiol tablets) provides an oral contraceptive regimen consisting of 24 light pink active film-coated tablets each containing 3 mg of drospirenone and 0.02 mg of ethinyl estradiol stabilized by betadex as a clathrate (molecular inclusion complex) and 4 white inert film coated tablets.

The inactive ingredients in the light pink tablets are lactose monohydrate NF, corn starch NF, magnesium stearate NF, hypromellose USP, talc USP, titanium dioxide USP, ferric oxide pigment, red NF. The white inert film-coated tablets contain lactose monohydrate NF, corn starch NF, povidone 25000 USP, magnesium stearate NF, hypromellose USP, talc USP, titanium dioxide USP.

Drospirenone (6R,7R,8R,9S,10R,13S,14S,15S,16S,17S)-1,3’,4’,6,6a,7,8,9,10,11, 12,13,14,15,15a,16-hexadecahydro-10,13-dimethylspiro-[17H-dicyclopropa- [6,7:15,16]cyclopenta[a]phenanthrene-17,2’(5H)-furan]-3,5’(2H)-dione) is a synthetic progestational compound and has a molecular weight of 366.5 and a molecular formula of C24H30O3.

Ethinyl estradiol (19-nor-17α-pregna 1,3,5(10)-triene-20-yne-3, 17-diol) is a synthetic estrogenic compound and has a molecular weight of 296.4 and a molecular formula of C20H24O2.

The structural formulas are as follows:

12 CLINICAL PHARMACOLOGY

12.1 Mechanism of Action

COCs lower the risk of becoming pregnant primarily by suppressing ovulation. Other possible mechanisms may include cervical mucus changes that inhibit sperm penetration and the endometrial changes that reduce the likelihood of implantation.

12.2 Pharmacodynamics

Drospirenone is a spironolactone analogue with antimineralocorticoid and antiandrogenic activity. The estrogen in Yaz is ethinyl estradiol.

Contraception

Two studies evaluated the effect of 3 mg DRSP / 0.02 mg EE combinations on the suppression of ovarian activity as assessed by measurement of follicle size via transvaginal ultrasound and serum hormone (progesterone and estradiol) analyses during two treatment cycles (21-day active tablet period plus 7-day pill-free period). More than 90% of subjects in these studies demonstrated ovulation inhibition. One study compared the effect of 3 mg DRSP/0.02 mg EE combinations with two different regimens (24-day active tablet period plus 4-day pill-free period vs. 21-day active tablet period plus 7-day pill-free period) on the suppression of ovarian activity during two treatment cycles. During the first treatment cycle, there were no subjects (0/49, 0%) taking the 24-day regimen who ovulated compared to 1 subject (1/50, 2%) using the 21-day regimen. After intentionally introduced dosing errors (3 missed active tablets on Days 1 to 3) during the second treatment cycle, there was 1 subject (1/49, 2%) taking the 24-day regimen who ovulated compared to 4 subjects (4/50, 8%) using the 21-day regimen.

Acne

Acne vulgaris is a skin condition with a multifactorial etiology including androgen stimulation of sebum production. While the combination of EE and DRSP increases sex hormone binding globulin (SHBG) and decreases free testosterone, the relationship between these changes and a decrease in the severity of facial acne in otherwise healthy women with this skin condition has not been established. The impact of the antiandrogenic activity of DRSP on acne is not known.

12.3 Pharmacokinetics

Absorption

The absolute bioavailability of DRSP from a single entity tablet is about 76%. The absolute bioavailability of EE is approximately 40% as a result of presystemic conjugation and first-pass metabolism. The absolute bioavailability of Yaz, which is a combination tablet of DRSP and EE stabilized by betadex as a clathrate (molecular inclusion complex), has not been evaluated. The bioavailability of EE is similar when dosed via a betadex clathrate formulation compared to when it is dosed as a free steroid. Serum concentrations of DRSP and EE reached peak levels within 1–2 hours after administration of Yaz.

The pharmacokinetics of DRSP are dose proportional following single doses ranging from 1–10 mg. Following daily dosing of Yaz, steady state DRSP concentrations were observed after 8 days. There was about 2 to 3 fold accumulation in serum Cmax and AUC (0–24h) values of DRSP following multiple dose administration of Yaz (see Table I).

For EE, steady-state conditions are reported during the second half of a treatment cycle. Following daily administration of Yaz, serum Cmax and AUC (0–24h) values of EE accumulate by a factor of about 1.5 to 2 (see Table I).

TABLE I: TABLE OF PHARMACOKINETIC PARAMETERS OF YAZ (DRSP 3 mg and EE 0.02 mg)
DRSP
Cycle / Day | No. of Subjects | Cmax [geometric mean (geometric coefficient of variation)] (ng/mL) | Tmax [median (range)] (h) | AUC(0–24h) (ng•h/mL) | t1/2 (h)
1/1 | 23 | 38.4 (25) | 1.5 (1–2) | 268 (19) | NA [NA = Not available]
1/21 | 23 | 70.3 (15) | 1.5 (1–2) | 763 (17) | 30.8 (22)
EE
Cycle / Day | No. of Subjects | Cmax (pg/mL) | Tmax (h) | AUC(0–24h) (pg•h/mL) | t1/2 (h)
1/1 | 23 | 32.8 (45) | 1.5 (1–2) | 108 (52) | NA
1/21 | 23 | 45.1 (35) | 1.5 (1–2) | 220 (57) | NA

Food Effect

The rate of absorption of DRSP and EE following single administration of a formulation similar to Yaz was slower under fed (high fat meal) conditions with the serum Cmax being reduced about 40% for both components. The extent of absorption of DRSP, however, remained unchanged. In contrast, the extent of absorption of EE was reduced by about 20% under fed conditions.

Distribution

DRSP and EE serum levels decline in two phases. The apparent volume of distribution of DRSP is approximately 4 L/kg and that of EE is reported to be approximately 4-5 L/kg.

DRSP does not bind to SHBG or corticosteroid binding globulin (CBG) but binds about 97% to other serum proteins. Multiple dosing over 3 cycles resulted in no change in the free fraction (as measured at trough levels). EE is reported to be highly but non-specifically bound to serum albumin (approximately 98.5 %) and induces an increase in the serum concentrations of both SHBG and CBG. EE induced effects on SHBG and CBG were not affected by variation of the DRSP dosage in the range of 2 to 3 mg.

Metabolism

The two main metabolites of DRSP found in human plasma were identified to be the acid form of DRSP generated by opening of the lactone ring and the 4,5-dihydrodrospirenone-3-sulfate. These metabolites were shown not to be pharmacologically active. In in vitro studies with human liver microsomes, DRSP was metabolized only to a minor extent mainly by Cytochrome P450 3A4 (CYP3A4).

EE has been reported to be subject to presystemic conjugation in both small bowel mucosa and the liver. Metabolism occurs primarily by aromatic hydroxylation but a wide variety of hydroxylated and methylated metabolites are formed. These are present as free metabolites and as conjugates with glucuronide and sulfate. CYP3A4 in the liver is responsible for the 2-hydroxylation which is the major oxidative reaction. The 2-hydroxy metabolite is further transformed by methylation and glucuronidation prior to urinary and fecal excretion.

Excretion

DRSP serum levels are characterized by a terminal disposition phase half-life of approximately 30 hours after both single and multiple dose regimens. Excretion of DRSP was nearly complete after ten days and amounts excreted were slightly higher in feces compared to urine. DRSP was extensively metabolized and only trace amounts of unchanged DRSP were excreted in urine and feces. At least 20 different metabolites were observed in urine and feces. About 38–47% of the metabolites in urine were glucuronide and sulfate conjugates. In feces, about 17–20% of the metabolites were excreted as glucuronides and sulfates.

For EE the terminal disposition phase half-life has been reported to be approximately 24 hours. EE is not excreted unchanged. EE is excreted in the urine and feces as glucuronide and sulfate conjugates and undergoes enterohepatic circulation.

Specific Populations

Pediatric Use: Safety and efficacy of Yaz has been established in women of reproductive age. Safety and efficacy are expected to be the same for postpubertal adolescents under the age of 18 and for users 18 years and older. Use of this product before menarche is not indicated. [See Use in Specific Populations (8.4).]

Geriatric Use: Yaz has not been studied in postmenopausal women and is not indicated in this population. [See Use in Specific Populations (8.5).]

Race: No clinically significant difference was observed between the pharmacokinetics of DRSP or EE in Japanese versus Caucasian women (age 25–35) when 3mg DRSP/0.02 mg EE was administered daily for 21 days. Other ethnic groups have not been specifically studied.

Renal Impairment: Yaz is contraindicated in patients with renal impairment.

The effect of renal impairment on the pharmacokinetics of DRSP (3 mg daily for 14 days) and the effect of DRSP on serum potassium levels were investigated in female subjects (n=28, age 30–65) with normal renal function and mild and moderate renal impairment. All subjects were on a low potassium diet. During the study, 7 subjects continued the use of potassium sparing drugs for the treatment of their underlying illness. On the 14th day (steady-state) of DRSP treatment, the serum DRSP levels in the group with mild renal impairment (creatinine clearance CLcr, 50–80 mL/min) were comparable to those in the group with normal renal function (CLcr, >80 mL/min). The serum DRSP levels were on average 37% higher in the group with moderate renal impairment (CLcr, 30–50 mL/min) compared to those in the group with normal renal function. DRSP treatment did not show any clinically significant effect on serum potassium concentration. Although hyperkalemia was not observed in the study, in five of the seven subjects who continued use of potassium sparing drugs during the study, mean serum potassium levels increased by up to 0.33 mEq/L. [See Contraindications (4), Warnings and Precautions (5.2) and Use in Specific Populations (8.6).]

Hepatic Impairment: Yaz is contraindicated in patients with hepatic disease.

The mean exposure to DRSP in women with moderate liver impairment is approximately three times higher than the exposure in women with normal liver function. Yaz has not been studied in women with severe hepatic impairment. [See Contraindications (4), Warnings and Precautions (5.4) and Use in Specific Populations (8.7).]

Drug Interactions

Effects of Other Drugs on Combined Hormonal Contraceptives

Substances diminishing the efficacy of COCs: Drugs or herbal products that induce certain enzymes, including CYP3A4, may decrease the effectiveness of COCs or increase breakthrough bleeding. [See Drug Interactions (7.1).]

Substances increasing the plasma levels of COCs:Co-administration of atorvastatin and certain COCs containing ethinyl estradiol increase AUC values for ethinyl estradiol by approximately 20%. Ascorbic acid and acetaminophen may increase plasma ethinyl estradiol levels, possibly by inhibition of conjugation. CYP3A4 inhibitors such as itraconazole or ketoconazole may increase plasma hormone levels. [See Drug Interactions (7.1).]

HIV protease inhibitors and non-nucleoside reverse transcriptase inhibitors:Significant changes (increase or decrease) in the plasma levels of estrogen and progestin have been noted in some cases of co-administration with HIV protease inhibitors or with non-nucleoside reverse transcriptase inhibitors. [See Drug Interactions (7.1).]

Antibiotics: There have been reports of pregnancy while taking hormonal contraceptives and antibiotics, but clinical pharmacokinetic studies have not shown consistent effects of antibiotics on plasma concentrations of synthetic steroids. [See Drug Interactions (7.1).]

Effects of Combined Oral Contraceptives on Other Drugs

COCs containing ethinyl estradiol may inhibit the metabolism of other compounds. COCs have been shown to significantly decrease plasma concentrations of lamotrigine, likely due to induction of lamotrigine glucuronidation. This may reduce seizure control; therefore, dosage adjustments of lamotrigine may be necessary. Consult the labeling of the concurrently-used drug to obtain further information about interactions with COCs or the potential for enzyme alterations. [See Drug Interactions (7.2).]

Metabolism of DRSP and potential effects of DRSP on hepatic cytochrome P450 (CYP) enzymes have been investigated in in vitro and in vivo studies. In in vitro studies DRSP did not affect turnover of model substrates of CYP1A2 and CYP2D6, but had an inhibitory influence on the turnover of model substrates of CYP1A1, CYP2C9, CYP2C19 and CYP3A4, with CYP2C19 being the most sensitive enzyme. The potential effect of DRSP on CYP2C19 activity was investigated in a clinical pharmacokinetic study using omeprazole as a marker substrate. In the study with 24 postmenopausal women [including 12 women with homozygous (wild type) CYP2C19 genotype and 12 women with heterozygous CYP2C19 genotype] the daily oral administration of 3 mg DRSP for 14 days did not affect the oral clearance of omeprazole (40 mg, single oral dose) and the CYP2C19 product 5-hydroxy omeprazole. Furthermore, no significant effect of DRSP on the systemic clearance of the CYP3A4 product omeprazole sulfone was found. These results demonstrate that DRSP did not inhibit CYP2C19 and CYP3A4 in vivo. [See Drug Interactions (7.2).]

Two additional clinical drug-drug interaction studies using simvastatin and midazolam as marker substrates for CYP3A4 were each performed in 24 healthy postmenopausal women. The results of these studies demonstrated that pharmacokinetics of the CYP3A4 substrates were not influenced by steady state DRSP concentrations achieved after administration of 3 mg DRSP/day. [See Drug Interactions (7.2).]

Interactions With Drugs That Have the Potential to Increase Serum Potassium

There is a potential for an increase in serum potassium in women taking Yaz with other drugs that may increase serum potassium [see Warnings and Precautions (5.2)].

A drug-drug interaction study of DRSP 3 mg/estradiol (E2) 1 mg versus placebo was performed in 24 mildly hypertensive postmenopausal women taking enalapril maleate 10 mg twice daily. Potassium levels were obtained every other day for a total of 2 weeks in all subjects. Mean serum potassium levels in the DRSP/E2 treatment group relative to baseline were 0.22 mEq/L higher that those in the placebo group. Serum potassium concentrations also were measured at multiple time points over 24 hours at baseline and on Day 14. On Day 14, the ratios for serum potassium Cmax and AUC in the DRSP/E2 group to those in the placebo group were 0.955 (90% CI: 0.914, 0.999) and 1.010 (90% CI: 0.944, 1.08), respectively. No patient in either treatment group developed hyperkalemia (serum potassium concentrations >5.5 mEq/L).

13 NONCLINICAL TOXICOLOGY

13.1 Carcinogenesis, Mutagenesis, Impairment of Fertility

In a 24 month oral carcinogenicity study in mice dosed with 10 mg/kg/day DRSP alone or 1 + 0.01, 3 + 0.03 and 10 + 0.1 mg/kg/day of DRSP and EE, 0.1 to 2 times the exposure (AUC of DRSP) of women taking a contraceptive dose, there was an increase in carcinomas of the harderian gland in the group that received the high dose of DRSP alone. In a similar study in rats given 10 mg/kg/day DRSP alone or 0.3 + 0.003, 3 + 0.03 and 10 + 0.1 mg/kg/day DRSP and EE, 0.8 to 10 times the exposure of women taking a contraceptive dose, there was an increased incidence of benign and malignant adrenal gland pheochromocytomas in the group receiving the high dose of DRSP. Mutagenesis studies for DRSP were conducted in vivo and in vitro and no evidence of mutagenic activity was observed.

14 CLINICAL STUDIES

14.1 Oral Contraceptive Clinical Trial

In the primary contraceptive efficacy study of Yaz (3 mg DRSP/0.02 mg EE) of up to 1 year duration, 1,027 subjects were enrolled and completed 11,480 28-day cycles of use. The age range was 17 to 36 years. The racial demographic was: 87.8% Caucasian, 4.6% Hispanic, 4.3% Black, 1.2% Asian, and 2.1% other. Women with a BMI greater than 35 were excluded from the trial. The pregnancy rate (Pearl Index) was 1.41 (95% CI [0.73, 2.47]) per 100 woman-years of use based on 12 pregnancies that occurred after the onset of treatment and within 14 days after the last dose of Yaz in women 35 years of age or younger during cycles in which no other form of contraception was used.

14.2 Premenstrual Dysphoric Disorder Clinical Trials

Two multicenter, double-blind, randomized, placebo-controlled studies were conducted to evaluate the effectiveness of Yaz in treating the symptoms of PMDD. Women aged 18–42 who met DSM-IV criteria for PMDD, confirmed by prospective daily ratings of their symptoms, were enrolled. Both studies measured the treatment effect of Yaz using the Daily Record of Severity of Problems scale, a patient-rated instrument that assesses the symptoms that constitute the DSM-IV diagnostic criteria. The primary study was a parallel group design that included 384 evaluable reproductive-aged women with PMDD who were randomly assigned to receive Yaz or placebo treatment for 3 menstrual cycles. The supportive study, a crossover design, was terminated prematurely prior to achieving recruitment goals due to enrollment difficulties. A total of 64 women of reproductive age with PMDD were treated initially with Yaz or placebo for up to 3 cycles followed by a washout cycle and then crossed over to the alternate medication for 3 cycles.

Efficacy was assessed in both studies by the change from baseline during treatment using a scoring system based on the first 21 items of the Daily Record of Severity of Problems. Each of the 21 items was rated on a scale from 1 (not at all) to 6 (extreme); thus a maximum score of 126 was possible. In both trials, women who received Yaz had statistically significantly greater improvement in their Daily Record of Severity of Problems scores. In the primary study, the average decrease (improvement) from baseline was 37.5 points in women taking Yaz, compared to 30.0 points in women taking placebo.

14.3 Acne Clinical Trials

In two multicenter, double-blind, randomized, placebo-controlled studies, 889 subjects, ages 14 to 45 years, with moderate acne received Yaz or placebo for six 28-day cycles. The primary efficacy endpoints were the percent change in inflammatory lesions, non-inflammatory lesions, total lesions, and the percentage of subjects with a "clear" or "almost clear" rating on the Investigator's Static Global Assessment (ISGA) scale on day 15 of cycle 6, as presented in Table II:

Table II: Efficacy Results for Acne Trials
 | Study 1 |  | Study 2
 | YAZ | Placebo | YAZ | Placebo
 | N=228 | N=230 | N=218 | N=213
ISGA Success Rate | 35 (15%) | 10 (4%) | 46 (21%) | 19 (9%)
Inflammatory Lesions; Mean Baseline Count; Mean Absolute (%) Reduction | 33; 15 (48%) | 33; 11 (32%) | 32; 16 (51%) | 32; 11 (34%)
Non-inflammatory Lesions; Mean Baseline Count; Mean Absolute (%) Reduction | 47; 18 (39%) | 47; 10 (18%) | 44; 17 (42%) | 44; 11 (26%)
Total lesions; Mean Baseline Count; Mean Absolute (%) Reduction | 80; 33 (42%) | 80; 21 (25%) | 76; 33 (46%) | 76; 22 (31%)

15 REFERENCES

1. Dinger JC, Heinemann LAJ, et al: The safety of a drospirenone-containing oral contraceptive: final results from the European active surveillance study on oral contraceptives based on 142,475 women-years of observation. Contraception 2007;75:344-354.

2. Seeger JD, Loughlin J, Eng PM, et al: Risk of thromboembolism in women taking ethinyl estradiol/drospirenone and other oral contraceptives. Obstetrics & Gynecology 2007;110(3):587-593.

3. van Hylckama Vlieg A, Helmerhorst FM, Vandenbroucke JP, et al: The venous thrombotic risk of oral contraceptives, effects of oestrogen dose and progestogen type: results of the MEGA case-control study. BMJ 2009;339:b2921.

4. Lidegaard O, Lokkegaard E, Svendsen AL, et al: Hormonal contraception and risk of venous thromboembolism: national follow-up study. BMJ 2009; 339:b2890.

16 HOW SUPPLIED/STORAGE AND HANDLING

16.1 How Supplied

Yaz (drospirenone/ethinyl estradiol tablets) are available in blister packs (NDC 54868-5828-0).

The film-coated tablets are rounded with biconvex faces, one side is embossed with DS or DP in a regular hexagon.

Each blister pack (28 film-coated tablets) contains in the following order:

- 24 active light pink round, unscored, film-coated tablets debossed with a "DS" in a regular hexagon on one side, each containing 3 mg drospirenone and 0.02 mg ethinyl estradiol
- 4 inert white round, unscored, film-coated tablets debossed with a "DP" in a regular hexagon on one side.

16.2 Storage Conditions

Store at 25°C (77°F); excursions permitted to 15–30°C (59–86°F) [see USP Controlled Room Temperature].

17 PATIENT COUNSELING INFORMATION

See FDA-approved patient labeling.

- Counsel patients that cigarette smoking increases the risk of serious cardiovascular events from COC use, and that women who are over 35 years old and smoke should not use COCs.
- Counsel patients that the increased risk of VTE compared to non-users of COCs is greatest after initially starting a COC or restarting (following a 4 week or greater pill-free interval) the same or a different COC.
- Counsel patients that Yaz does not protect against HIV-infection (AIDS) and other sexually transmitted diseases.
- Counsel patients on Warnings and Precautions associated with COCs.
- Counsel patients that Yaz contains DRSP. Drospirenone may increase potassium. Patients should be advised to inform their healthcare provider if they have kidney, liver or adrenal disease because the use of Yaz in the presence of these conditions could cause serious heart and health problems. They should also inform their healthcare provider if they are currently on daily, long-term treatment (NSAIDs, potassium-sparing diuretics, potassium supplementation, ACE inhibitors, angiotensin-II receptor antagonists, heparin or aldosterone antagonists) for a chronic condition.
- Yaz is not indicated during pregnancy. If pregnancy is planned or occurs during treatment with Yaz, further intake must be stopped.
- Counsel patients to take one tablet daily by mouth at the same time every day. Instruct patients what to do in the event pills are missed. See "WHAT TO DO IF YOU MISS PILLS" section in FDA-APPROVED PATIENT LABELING.
- Counsel patients to use a back-up or alternative method of contraception when enzyme inducers are used with COCs.
- Counsel patients who are breastfeeding or who desire to breastfeed that COCs may reduce breast milk production. This is less likely to occur if breastfeeding is well established.
- Counsel any patient who starts COCs postpartum, and who have not yet had a period, to use an additional method of contraception until she has taken a light pink tablet for 7 consecutive days.
- Counsel patients that amenorrhea may occur. Rule out pregnancy in the event of amenorrhea in two or more consecutive cycles.

FDA Approved Patient Labeling

Guide for Using Yaz

WARNING TO WOMEN WHO SMOKE

Do not use Yaz if you smoke cigarettes and are over 35 years old. Smoking increases your risk of serious cardiovascular side effects (heart and blood vessel problems) from birth control pills, including death from heart attack, blood clots or stroke. This risk increases with age and the number of cigarettes you smoke.

Birth control pills help to lower the chances of becoming pregnant when taken as directed. They do not protect against HIV infection (AIDS) and other sexually transmitted diseases.

What Is Yaz?

Yaz is a birth control pill. It contains two female hormones, a synthetic estrogen called ethinyl estradiol and a progestin called drospirenone.

The progestin drospirenone may increase potassium. Therefore, you should not take Yaz if you have kidney, liver or adrenal disease because this could cause serious heart and health problems. Other drugs may also increase potassium. If you are currently on daily, long-term treatment for a chronic condition with any of the medications below, you should consult your healthcare provider about whether Yaz is right for you, and during the first month that you take Yaz, you should have a blood test to check your potassium level.

- NSAIDs (ibuprofen [Motrin, Advil], naproxen [Aleve and others] when taken long-term and daily for treatment of arthritis or other problems)
- Potassium-sparing diuretics (spironolactone and others)
- Potassium supplementation
- ACE inhibitors (Capoten, Vasotec, Zestril and others)
- Angiotensin-II receptor antagonists (Cozaar, Diovan, Avapro and others)
- Heparin
- Aldosterone antagonists

Yaz may also be taken to treat premenstrual dysphoric disorder (PMDD) if you choose to use the Pill for birth control. Unless you have already decided to use the Pill for birth control, you should not start Yaz to treat your PMDD because there are other medical therapies for PMDD that do not have the same risks as the Pill. PMDD is a mood disorder related to the menstrual cycle. PMDD significantly interferes with work or school, or with usual social activities and relationships with others. Symptoms include markedly depressed mood, anxiety or tension, mood swings, and persistent anger or irritability. Other features include decreased interest in usual activities, difficulty concentrating, lack of energy, change in appetite or sleep, and feeling out of control. Physical symptoms associated with PMDD may include breast tenderness, headache, joint and muscle pain, bloating and weight gain. These symptoms occur regularly before menstruation starts and go away within a few days following the start of the period. Diagnosis of PMDD should be made by healthcare providers.

You should only use Yaz for treatment of PMDD if you:

- Have already decided to use oral contraceptives for birth control, and
- Have been diagnosed with PMDD by your healthcare provider.

Yaz has not been shown to be effective for the treatment of premenstrual syndrome (PMS), a less serious set of symptoms occurring before menstruation. If you or your healthcare provider believe you have PMS, you should take Yaz only if you want to prevent pregnancy; and not for the treatment of PMS.

Yaz may also be taken to treat moderate acne if all of the following are true:

- Your healthcare provider says it is safe for you to use Yaz.
- You are at least 14 years old.
- You have started having menstrual periods.
- You want to use a birth control pill to prevent pregnancy.

How Well Does Yaz Work?

Your chance of getting pregnant depends on how well you follow the directions for taking your birth control pills. The better you follow the directions, the less chance you have of getting pregnant.

Based on the results of one clinical study, 1 to 2 women out of 100 women, may get pregnant during the first year they use Yaz.

The following chart shows the chance of getting pregnant for women who use different methods of birth control. Each box on the chart contains a list of birth control methods that are similar in effectiveness. The most effective methods are at the top of the chart. The box on the bottom of the chart shows the chance of getting pregnant for women who do not use birth control and are trying to get pregnant.

How Do I Take Yaz?

1. Be sure to read these directions before you start taking your pills or anytime you are not sure what to do.

2. The right way to take the pill is to take one pill every day at the same time in the order directed on the package. Preferably, take the pill after the evening meal or at bedtime, with some liquid, as needed. Yaz can be taken without regard to meals.

If you miss pills you could get pregnant. This includes starting the pack late. The more pills you miss, the more likely you are to get pregnant. See "WHAT TO DO IF YOU MISS PILLS” below.

3. Many women have spotting or light bleeding at unexpected times, or may feel sick to their stomach during the first 1-3 packs of pills.

If you do have spotting or light bleeding or feel sick to your stomach, do not stop taking the pill. The problem will usually go away. If it does not go away, check with your healthcare provider.

4. Missing pills can also cause spotting or light bleeding, even when you make up these missed pills.

On the days you take two pills, to make up for missed pills, you could also feel a little sick to your stomach.

5. If you have vomiting (within 3 to 4 hours after you take your pill), you should follow the instructions for "WHAT TO DO IF YOU MISS PILLS." If you have diarrhea or if you take certain medicines, including some antibiotics and some herbal products such as St. John's Wort, your pills may not work as well.

Use a back-up method (such as condoms and spermicides) until you check with your healthcare provider.

6. If you have trouble remembering to take the pill, talk to your healthcare provider about how to make pill-taking easier or about using another method of birth control.

7. If you have any questions or are unsure about the information in this leaflet, call your healthcare provider.

Before You Start Taking Your Pills

1. Decide What Time of Day You Want to Take Your Pill

It is important to take Yaz in the order directed on the package at the same time every day, preferably after the evening meal or at bedtime, with some liquid, as needed. Yaz can be taken without regard to meals.

2. Look at Your Pill Pack - It has 28 Pills

The Yaz-pill pack has 24 light pink pills (with hormones) to be taken for 24 days, followed by 4 white pills (without hormones) to be taken for the next four days.

3. Also look for:

a) Where on the pack to start taking pills,

b) In what order to take the pills (follow the arrows)

4. Be sure you have ready at all times (a) another kind of birth control (such as condoms and spermicides) to use as a back-up in case you miss pills, and (b) an extra, full pill pack.

When To Start the First Pack of Pills

You have a choice for which day to start taking your first pack of pills. Decide with your healthcare provider which is the best day for you. Pick a time of day which will be easy to remember.

Day 1 Start:

1. Take the first light pink pill of the pack during the first 24 hours of your period.

2. You will not need to use a back-up method of birth control, since you are starting the Pill at the beginning of your period. However, if you start Yaz later than the first day of your period, you should use another method of birth control (such as a condom and spermicide) as a back-up method until you have taken 7 light pink pills.

Sunday Start:

1. Take the first light pink pill of the pack on the Sunday after your period starts, even if you are still bleeding. If your period begins on Sunday, start the pack that same day.

2. Use another method of birth control (such as a condom and spermicide) as a back-up method if you have sex anytime from the Sunday you start your first pack until the next Sunday (7 days). This also applies if you start Yaz after having been pregnant, and you have not had a period since your pregnancy.

When You Switch From a Different Birth Control Pill

When switching from another birth control pill, Yaz should be started on the same day that a new pack of the previous birth control pill would have been started.

When You Switch From Another Type of Birth Control Method

When switching from a transdermal patch or vaginal ring, Yaz should be started when the next application would have been due. When switching from an injection, Yaz should be started when the next dose would have been due. When switching from an intrauterine contraceptive or an implant, Yaz should be started on the day of removal.

What to Do During the Month

1. Take one pill at the same time every day until the pack is empty.

Do not skip pills even if you are spotting or bleeding between monthly periods or feel sick to your stomach (nausea).

Do not skip pills even if you do not have sex very often.

2. When you finish a pack of pills, start the next pack on the day after your last white pill. Do not wait any days between packs.

What to Do if You Miss Pills

If you miss 1 light pink pill of your pack:

1. Take it as soon as you remember. Take the next pill at your regular time. This means you may take two pills in one day.

2. You do not need to use a back-up birth control method if you have sex.

If you miss 2 light pink pills in a row in Week 1 or Week 2 of your pack:

1. Take two pills on the day you remember and two pills the next day.

2. Then take one pill a day until you finish the pack.

3. You could become pregnant if you have sex in the 7 days after you restart your pills. You must use another birth control method (such as a condom and spermicide) as a back-up for those 7 days.

If you miss 2 light pink pills in a row in Week 3 or Week 4 of your pack:

1. If you are a Day 1 Starter:

Throw out the rest of the pill pack and start a new pack that same day.

If you are a Sunday Starter:

Keep taking one pill every day until Sunday. On Sunday, throw out the rest of the pack and start a new pack of pills that same day.

2. You could become pregnant if you have sex in the 7 days after you restart your pills. You must use another birth control method (such as a condom and spermicide) as a back-up for those 7 days.

3. You may not have your period this month but this is expected. However, if you miss your period two months in a row, call your healthcare provider because you might be pregnant.

If you miss 3 or more light pink pills in a row during any week:

1. If you are a Day 1 Starter:

Throw out the rest of the pill pack and start a new pack that same day.

If you are a Sunday Starter:

Keep taking 1 pill every day until Sunday. On Sunday, throw out the rest of the pack and start a new pack of pills that same day.

2. You could become pregnant if you have sex in the 7 days after you restart your pills. You must use another birth control method (such as condoms and spermicides) as a back-up for those 7 days.

3. Call your healthcare provider if you miss your period, because you might be pregnant.

If you miss any of the 4 white pills in Week 4:

Throw away the pills you missed.

Keep taking one pill each day until the pack is empty.

You do not need a back-up method.

Finally, if you are still not sure what to do about the pills you have missed:

Use a back-up method (such as condoms and spermicides) anytime you have sex.

Contact your healthcare provider and continue taking one active light pink pill each day until otherwise directed.

WHO SHOULD NOT TAKE Yaz?

Your healthcare provider will not give you Yaz if you:

• Ever had blood clots in your legs (deep vein thrombosis), lungs (pulmonary embolism), or eyes (retinal thrombosis)

• Ever had a stroke

• Ever had a heart attack

• Have certain heart valve problems or heart rhythm abnormalities that can cause blood clots to form in the heart

o Have an inherited problem with your blood that makes it clot more than normal

• Have high blood pressure that medicine can’t control

• Have diabetes with kidney, eye, nerve, or blood vessel damage

• Ever had certain kinds of severe migraine headaches with aura, numbness, weakness or changes in vision

o Ever had breast cancer or any cancer that is sensitive to female hormones

• Have liver disease, including liver tumors

• Have kidney disease

• Have adrenal disease

Also, do not take birth control pills if you:

• Smoke and are over 35 years old

• Are or suspect you are pregnant

Birth control pills may not be a good choice for you if you have ever had jaundice (yellowing of the skin or eyes) caused by pregnancy (also called cholestasis of pregnancy).

Tell your healthcare provider if you have ever had any of the above conditions (your healthcare provider can recommend another method of birth control).

What Else Should I Know about Taking Yaz?

Birth control pills do not protect you against any sexually transmitted disease, including HIV, the virus that causes AIDS.

Do not skip any pills, even if you do not have sex often.

If you miss a period, you could be pregnant. However, some women miss periods or have light periods on birth control pills, even when they are not pregnant. Contact your healthcare provider for advice if you:

- Think you are pregnant
- Miss one period and have not taken your birth control pills every day
- Miss two periods in a row

Birth control pills should not be taken during pregnancy. However, birth control pills taken by accident during pregnancy are not known to cause birth defects.

You should stop Yaz at least four weeks before you have major surgery and not restart it until at least two weeks after the surgery due to an increased risk of blood clots.

If you are breastfeeding, consider another birth control method until you are ready to stop breastfeeding. Birth control pills that contain estrogen, like Yaz, may decrease the amount of milk you make. A small amount of the pill's hormones pass into breast milk.

If you are currently on daily, long-term treatment for a chronic condition with any of the following medications, you should consult your healthcare provider before taking Yaz:

- NSAIDs (ibuprofen, naproxen and others)
- Potassium-sparing diuretics (spironolactone and others)
- Potassium supplementation
- ACE inhibitors (captopril, enalapril, lisinopril and others)
- Angiotensin-II receptor antagonists (Cozaar, Diovan, Avapro and others)
- Heparin
- Aldosterone antagonists

Tell your healthcare provider about all medicines and herbal products that you take. Some other medicines and herbal products may make birth control pills less effective, including:

- Barbiturates
- Bosentan
- Carbamazepine
- Felbamate
- Griseofulvin
- Oxcarbazepine
- Phenytoin
- Rifampin
- St. John’s wort
- Topiramate

Consider using another birth control method when you take medicines that may make birth control pills less effective.

Birth control pills may interact with lamotrigine, an anticonvulsant used for epilepsy. This may increase the risk of seizures, so your healthcare provider may need to adjust the dose of lamotrigine.

If you have vomiting or diarrhea, your birth control pills may not work as well. Use another birth control method, like condoms and a spermicide, until you check with your healthcare provider.

If you are scheduled for any laboratory tests, tell your doctor you are taking birth-control pills. Certain blood tests may be affected by birth-control pills.

What are the Most Serious Risks of Taking Birth Control Pills?

Like pregnancy, birth control pills increase the risk of serious blood clots, especially in women who have other risk factors, such as smoking, obesity, or age greater than 35. This increased risk is highest when you first start taking birth control pills and when you restart the same or different birth control pills after not using them for a month or more.

It is possible to die from a problem caused by a blood clot, such as a heart attack or a stroke. Some examples of serious clots are blood clots in the:

- Legs (thrombophlebitis)
- Lungs (pulmonary embolus)
- Eyes (loss of eyesight)
- Heart (heart attack)
- Brain (stroke)

A few women who take birth control pills may get:

- High blood pressure
- Gallbladder problems
- Rare cancerous or noncancerous liver tumors
  All of these events are uncommon in healthy women.

Call your healthcare provider right away if you have:

- Persistent leg pain
- Sudden shortness of breath
- Sudden blindness, partial or complete
- Severe pain in your chest
- Sudden, severe headache unlike your usual headaches
- Weakness or numbness in an arm or leg, or trouble speaking
- Yellowing of the skin or eyeballs
  What are the Common Side Effects of Birth Control Pills?

The most common side effects of birth control pills are:

- Spotting or bleeding between menstrual periods
- Nausea
- Breast tenderness
- Headache

These side effects are usually mild and usually disappear with time.

Less common side effects are:

- Acne
- Less sexual desire
- Bloating or fluid retention
- Blotchy darkening of the skin, especially on the face
- High blood sugar, especially in women who already have diabetes
- High fat (cholesterol; triglyceride) levels in the blood
- Depression, especially if you have had depression in the past. Call your healthcare provider immediately if you have any thoughts of harming yourself.
- Problems tolerating contact lenses
- Weight changes

This is not a complete list of possible side effects. Talk to your healthcare provider if you develop any side effects that concern you. You may report side effects to the FDA at 1-800-FDA-1088.

No serious problems have been reported from a birth control pill overdose, even when accidentally taken by children.

Do Birth Control Pills Cause Cancer?

Birth control pills do not seem to cause breast cancer. However, if you have breast cancer now, or have had it in the past, do not use birth control pills because some breast cancers are sensitive to hormones.

Women who use birth control pills may have a slightly higher chance of getting cervical cancer. However, this may be due to other reasons such as having more sexual partners.

What Should I Know about My Period when Taking Yaz?

Irregular vaginal bleeding or spotting may occur while you are taking Yaz. Irregular bleeding may vary from slight staining between menstrual periods to breakthrough bleeding, which is a flow much like a regular period. Irregular bleeding occurs most often during the first few months of oral contraceptive use, but may also occur after you have been taking the pill for some time. Such bleeding may be temporary and usually does not indicate any serious problems. It is important to continue taking your pills on schedule. If the bleeding occurs in more than one cycle, is unusually heavy, or lasts for more than a few days, call your healthcare provider.

Some women may not have a menstrual period but this should not be cause for alarm as long has you have taken the pills according to direction.

What if I Miss My Scheduled Period when Taking Yaz?

It is not uncommon to miss your period. However, if you miss two periods in a row or miss one period when you have not taken your birth control pills according to directions, call your healthcare provider. Also notify your healthcare provider if you have symptoms of pregnancy such as morning sickness or unusual breast tenderness. It is important that your healthcare provider checks you to find out if you are pregnant. Stop taking Yaz if you are pregnant.

What If I Want to Become Pregnant?

You may stop taking the pill whenever you wish. Consider a visit with your healthcare provider for a pre-pregnancy checkup before you stop taking the pill.

General Advice about Yaz

Your healthcare provider prescribed Yaz for you. Please do not share Yaz with anyone else. Keep Yaz out of the reach of children.

If you have concerns or questions, ask your healthcare provider. You may also ask your healthcare provider for a more detailed label written for medical professionals.

Manufactured for

Bayer HealthCare Pharmaceuticals Inc.

Wayne, NJ 07470

Manufactured in Germany

©2011 Bayer HealthCare Pharmaceuticals Inc. All Rights Reserved.

Additional barcode labeling by:
Physicians Total Care, Inc.
Tulsa, Oklahoma 74146

PACKAGE LABEL

YAZ Individual Trade Carton

NDC 54868-5828-0 1 Unit

Rx only

This product (like all oral contraceptives) is intended to prevent pregnancy. It does not protect against HIV infection (AIDS) and other sexually transmitted diseases.

YAZ®

(drospirenone & ethinyl estradiol)

3 mg /0.02 mg

28 tablets

oral